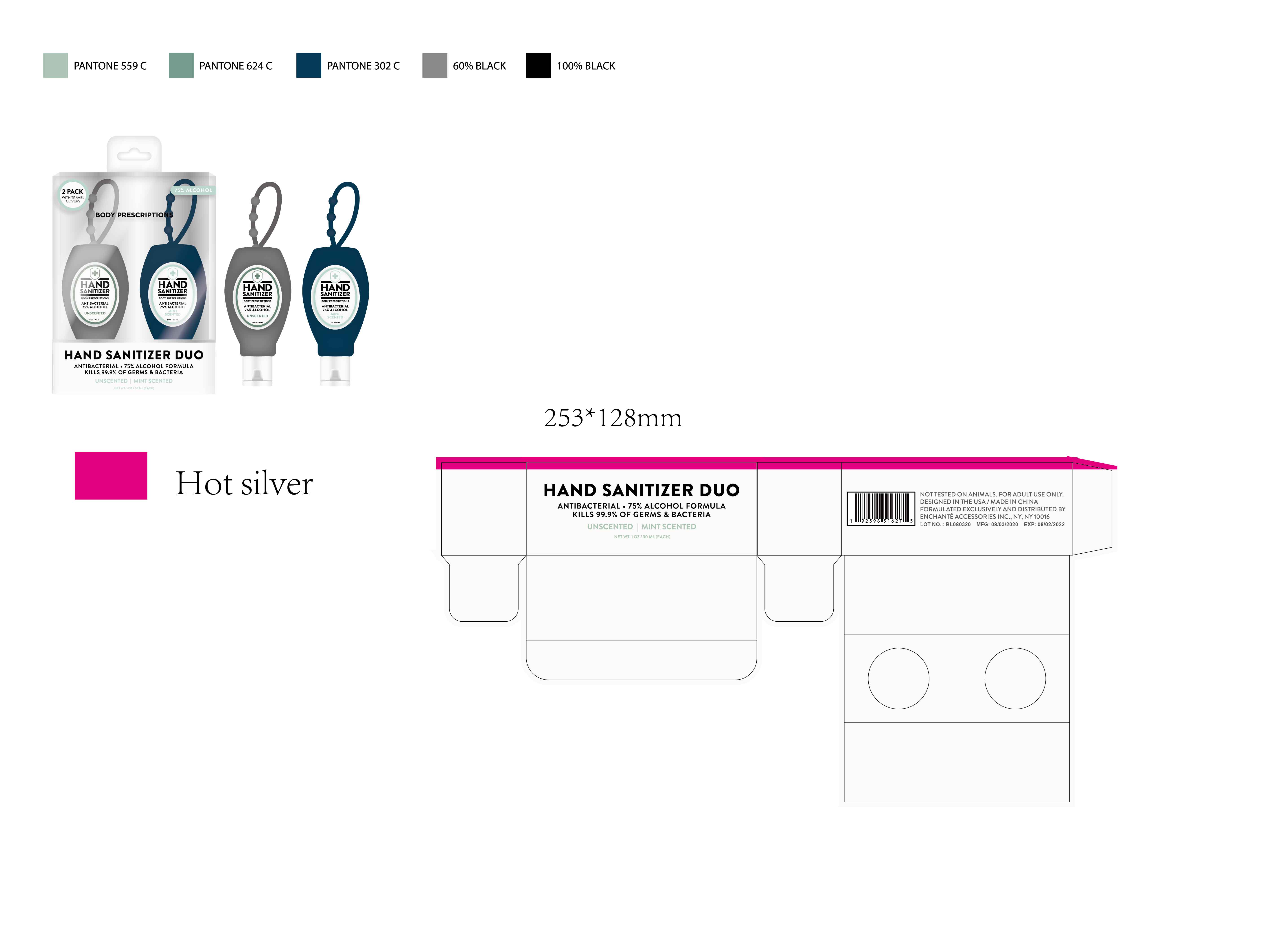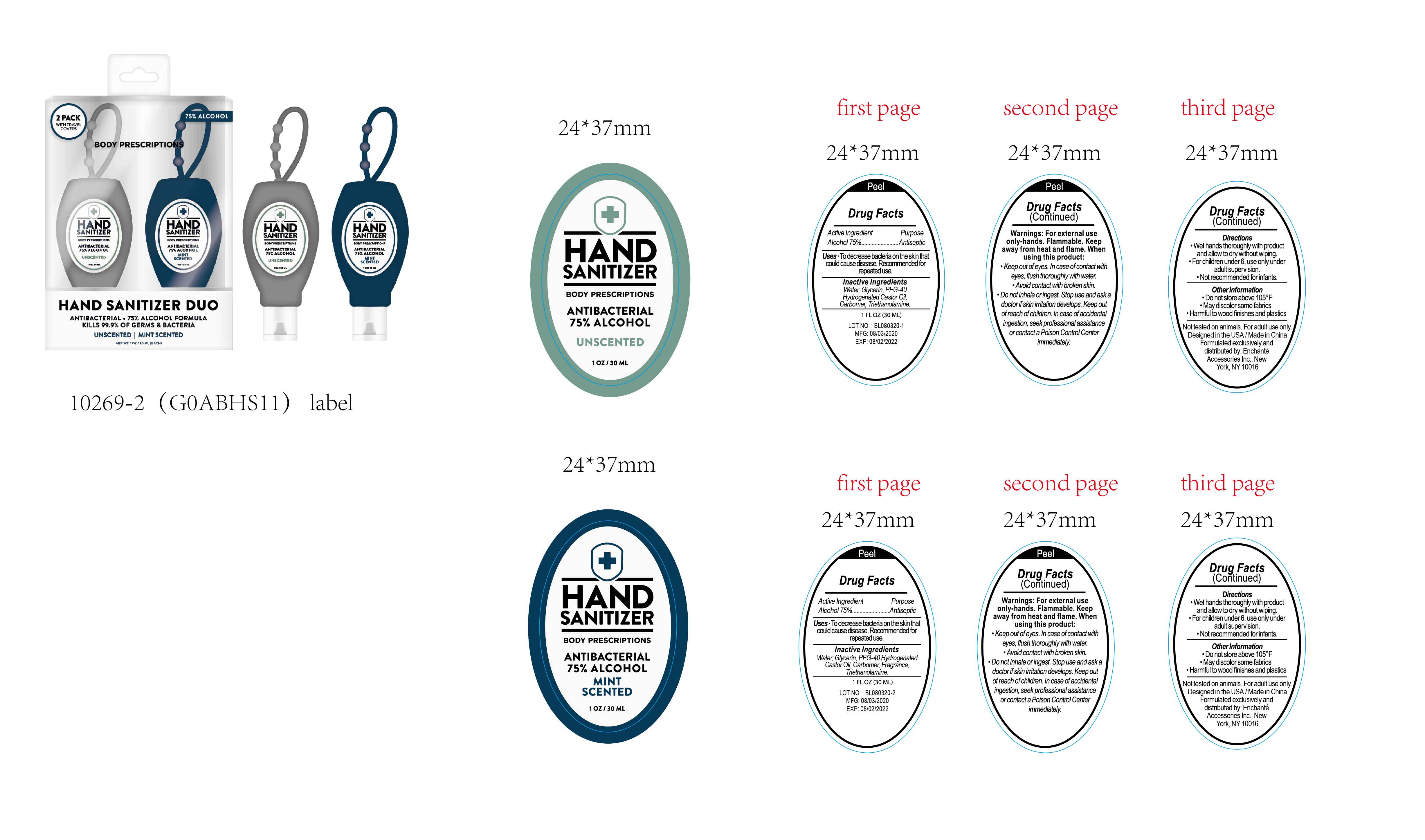 DRUG LABEL: BODY PRESCRIPTIONS ANTIBACTERIAL HAND SANITIZER DUO UNSCENTED MINT SCENTED
NDC: 50563-252 | Form: KIT | Route: TOPICAL
Manufacturer: ENCHANTE ACCESSORIES INC.
Category: otc | Type: HUMAN OTC DRUG LABEL
Date: 20200916

ACTIVE INGREDIENTS: ALCOHOL 75 mL/100 mL; ALCOHOL 75 mL/100 mL
INACTIVE INGREDIENTS: WATER; GLYCERIN; CARBOMER 940; TROLAMINE; WATER; GLYCERIN; CARBOMER 940; TROLAMINE

50563-250-251-252/ G0ABHS11

BODY PRESCRIPTIONS ANTIBACTERIAL HAND SANITIZER Unscented

Active Ingredient

Alcohol 75%

Purpose

Antiseptic

Use

■ To decrease bacteria on the skin that could cause disease
■Recommended for repeated use

WARNINGS

For external use only, Hands

Flammable. Keep away from heat and flame

When using this product, keep out of eyes.
In case of contact with eyes, flush thoroughly with water

Avoid contact with broken skin

Do not inhale or ingest

Stop Use

Stop use and ask a doctor if skin irritation develops

Keep out of reach of children. In case of accidental ingestion, seek professional assistance or contact a poison control center immediately

Directions

Wet hands thoroughly with product and allow to dry without wiping

For children under 6, use only under adult supervision

Not recommended for infants

Other information

Do not store above 105F

May discolor some fabrics

Harmful to wood finishes and plastics

Inactive ingredients

Water, Glycerin, PEG-40 Hydrogenated Castor Oil, Carbomer, Triethanolamine

BODY PRESCRIPTIONS ANTIBACTERIAL HAND SANITIZER MINT SCENTED

Active Ingredient

Alcohol 75%

Purpose:

Antiseptic

Uses:

To decrease bacteria on the skin that could cause disease
■Recommended for repeated use

Warnings

For external use only, Hands

Flammable. Keep away from heat and flame

When using this product, keep out of eyes.
In case of contact with eyes, flush thoroughly with water

Avoid contact with broken skin

Do not inhale or ingest

Stop Use

Stop use and ask a doctor if skin irritation develops

Keep out of reach of children. In case of accidental ingestion, seek professional assistance or contact a poison control center immediately

Directions

Wet hands thoroughly with product and allow to dry without wiping

For children under 6, use only under adult supervision

Not recommended for infants

Other Information

Do not store above 105F

May discolor some fabrics

Harmful to wood finishes and plastics

Inactive Ingredients

Water, Glycerin, PEG-40 Hydrogenated Castor Oil, Carbomer, Fragrance, Triethanolamine